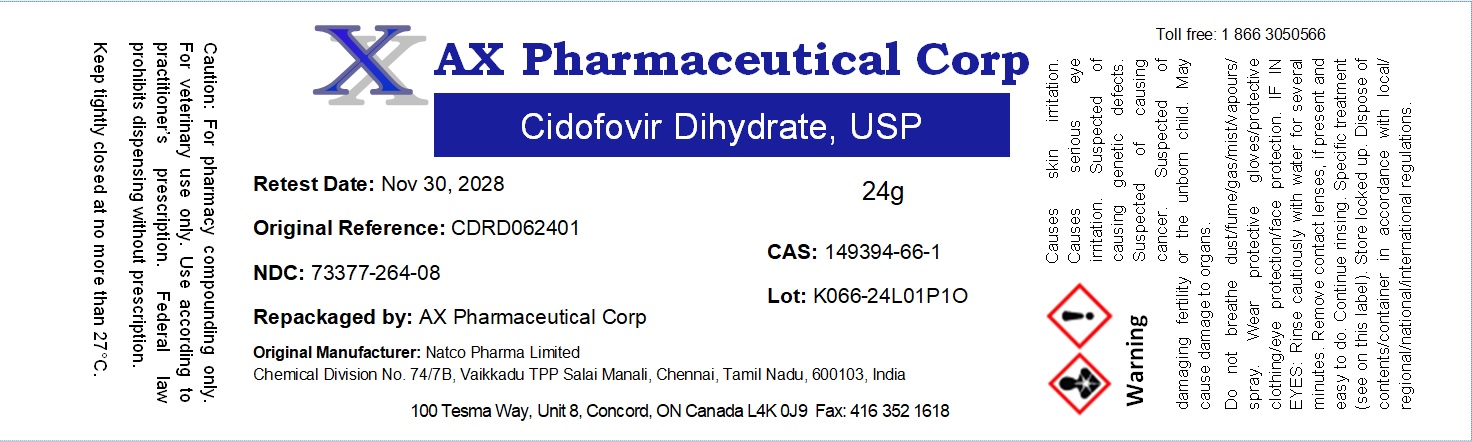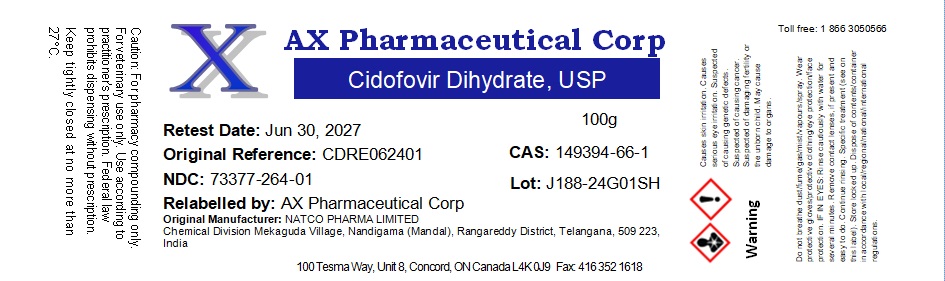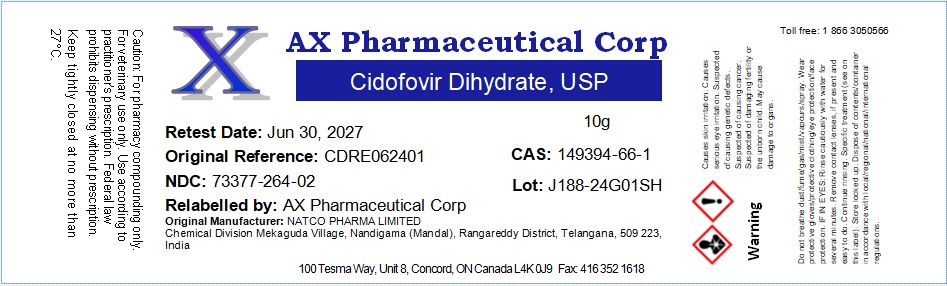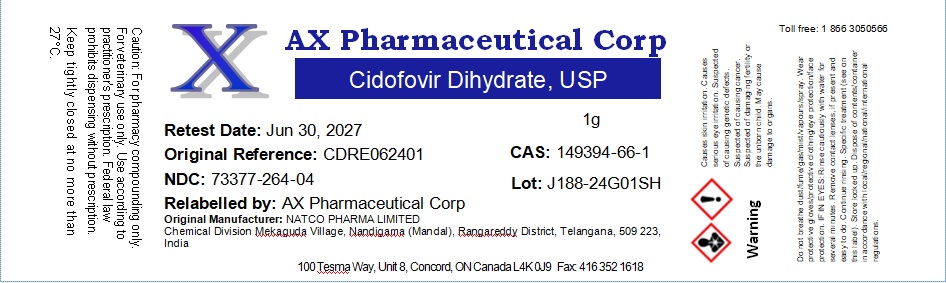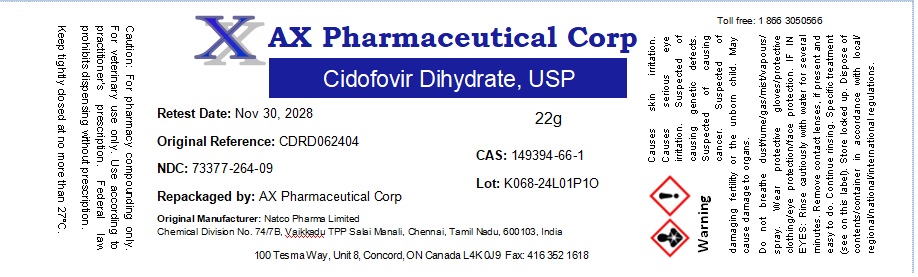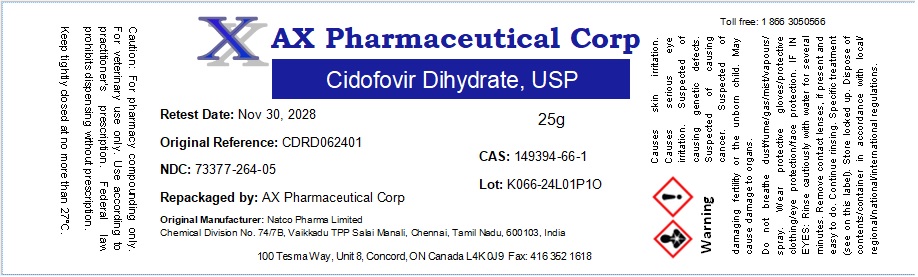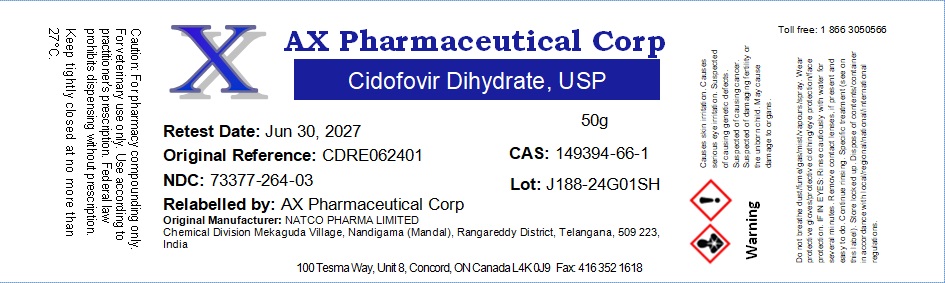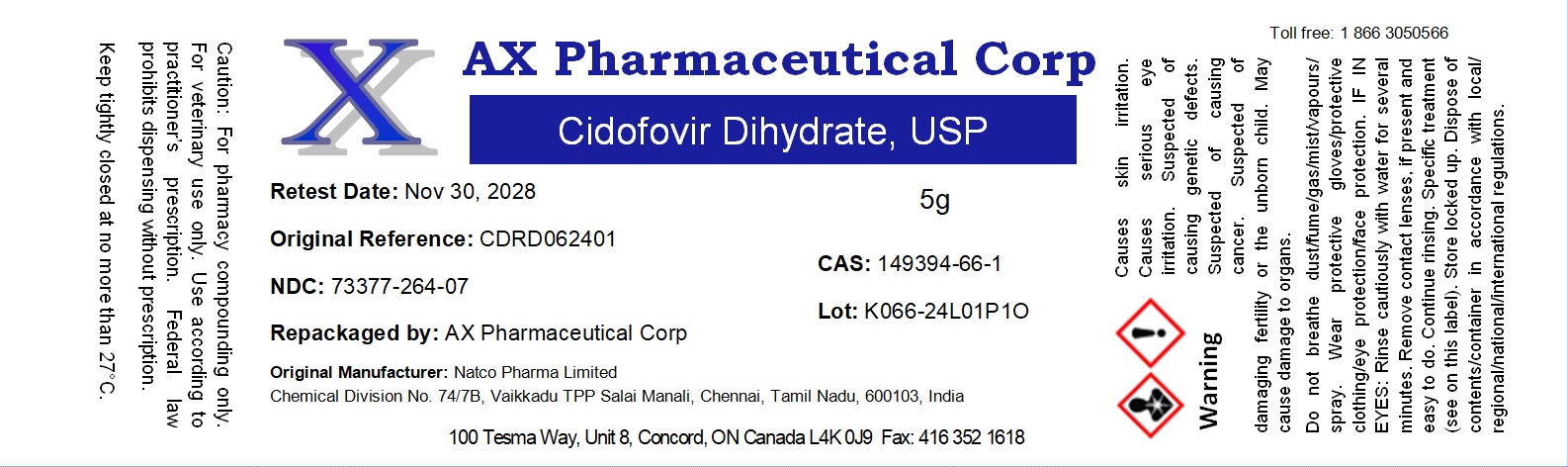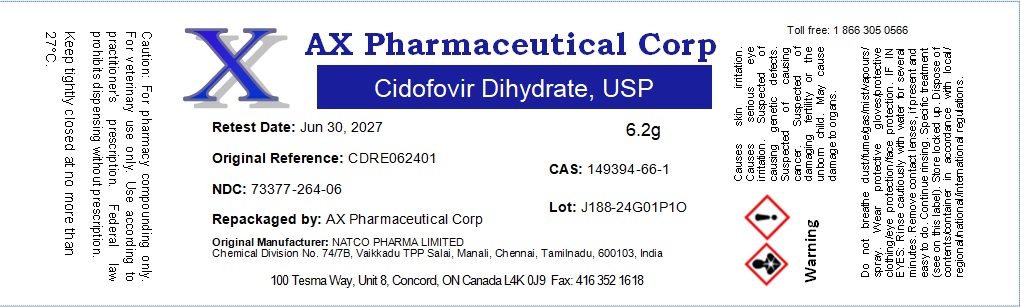 DRUG LABEL: Cidofovir Dihydrate
NDC: 73377-264 | Form: POWDER
Manufacturer: AX Pharmaceutical Corp
Category: other | Type: BULK INGREDIENT - ANIMAL DRUG
Date: 20250407

ACTIVE INGREDIENTS: CIDOFOVIR 1 g/1 g

Cidofovir Dihydrate